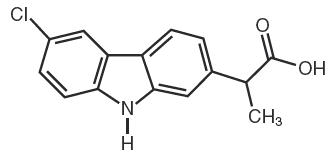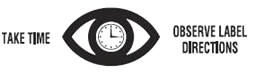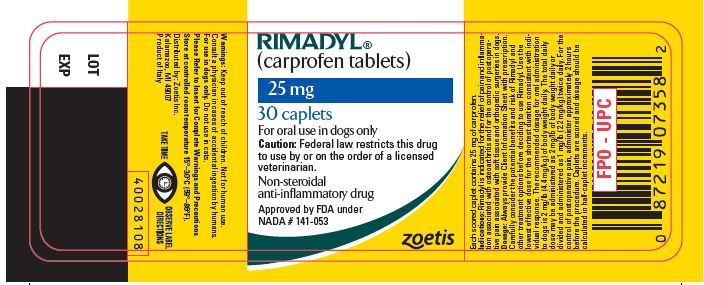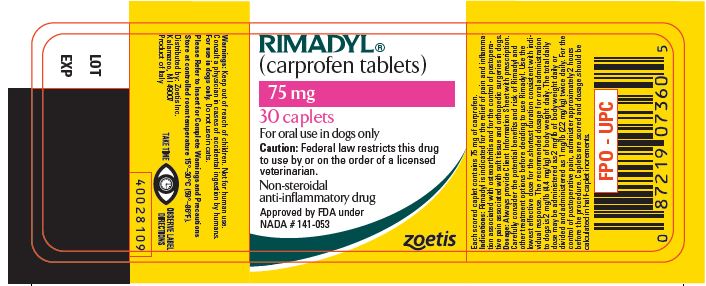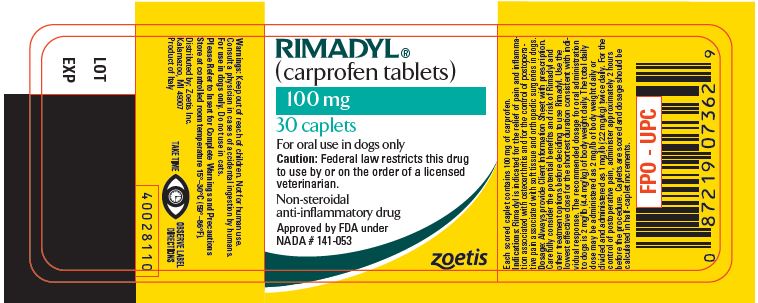 DRUG LABEL: Rimadyl
NDC: 54771-8461 | Form: TABLET
Manufacturer: Zoetis Inc.
Category: animal | Type: PRESCRIPTION ANIMAL DRUG LABEL
Date: 20191001

ACTIVE INGREDIENTS: CARPROFEN 25 mg/1 1

RIMADYL®
(carprofen)

Caplets

Non-steroidal anti-inflammatory drug

For oral use in dogs only

CAUTION

Federal law restricts this drug to use by or on the order of a licensed veterinarian.

DESCRIPTION

Rimadyl (carprofen) is a non-steroidal anti-inflammatory drug (NSAID) of the propionic acid class that includes ibuprofen, naproxen, and ketoprofen. Carprofen is the nonproprietary designation for a substituted carbazole, 6-chloro-α-methyl-9H-carbazole-2-acetic acid. The empirical formula is C15H12ClNO2 and the molecular weight 273.72. The chemical structure of carprofen is:

Carprofen is a white, crystalline compound. It is freely soluble in ethanol, but practically insoluble in water at 25°C.

CLINICAL PHARMACOLOGY

Carprofen is a non-narcotic, non-steroidal anti-inflammatory agent with characteristic analgesic and antipyretic activity approximately equipotent to indomethacin in animal models.^1

The mechanism of action of carprofen, like that of other NSAIDs, is believed to be associated with the inhibition of cyclooxygenase activity. Two unique cyclooxygenases have been described in mammals.^2 The constitutive cyclooxygenase, COX-1, synthesizes prostaglandins necessary for normal gastrointestinal and renal function. The inducible cyclooxygenase, COX-2, generates prostaglandins involved in inflammation. Inhibition of COX-1 is thought to be associated with gastrointestinal and renal toxicity while inhibition of COX-2 provides anti-inflammatory activity. The specificity of a particular NSAID for COX-2 versus COX-1 may vary from species to species.^3 In an in vitro study using canine cell cultures, carprofen demonstrated selective inhibition of COX-2 versus COX-1.^4 Clinical relevance of these data has not been shown. Carprofen has also been shown to inhibit the release of several prostaglandins in two inflammatory cell systems: rat polymorphonuclear leukocytes (PMN) and human rheumatoid synovial cells, indicating inhibition of acute (PMN system) and chronic (synovial cell system) inflammatory reactions.^1

Several studies have demonstrated that carprofen has modulatory effects on both humoral and cellular immune responses.^5–9 Data also indicate that carprofen inhibits the production of osteoclast-activating factor (OAF), PGE1, and PGE2 by its inhibitory effects on prostaglandin biosynthesis.^1

Based upon comparison with data obtained from intravenous administration, carprofen is rapidly and nearly completely absorbed (more than 90% bioavailable) when administered orally.^10 Peak blood plasma concentrations are achieved in 1–3 hours after oral administration of 1, 5, and 25 mg/kg to dogs. The mean terminal half-life of carprofen is approximately 8 hours (range 4.5–9.8 hours) after single oral doses varying from 1–35 mg/kg of body weight. After a 100 mg single intravenous bolus dose, the mean elimination half-life was approximately 11.7 hours in the dog. Rimadyl is more than 99% bound to plasma protein and exhibits a very small volume of distribution.

Carprofen is eliminated in the dog primarily by biotransformation in the liver followed by rapid excretion of the resulting metabolites (the ester glucuronide of carprofen and the ether glucuronides of 2 phenolic metabolites, 7-hydroxy carprofen and 8-hydroxy carprofen) in the feces (70–80%) and urine (10–20%). Some enterohepatic circulation of the drug is observed.

INDICATIONS

Rimadyl is indicated for the relief of pain and inflammation associated with osteoarthritis and for the control of postoperative pain associated with soft tissue and orthopedic surgeries in dogs.

CONTRAINDICATIONS

Rimadyl should not be used in dogs exhibiting previous hypersensitivity to carprofen.

WARNINGS

Keep out of reach of children. Not for human use. Consult a physician in cases of accidental ingestion by humans. For use in dogs only. Do not use in cats.

All dogs should undergo a thorough history and physical examination before initiation of NSAID therapy.
Appropriate laboratory tests to establish hematological and serum biochemical baseline data prior to, and periodically during, administration of any NSAID should be considered. Owners should be advised to observe for signs of potential drug toxicity (see Information for Dog Owners, Adverse Reactions, Animal Safety and Post-Approval Experience).

PRECAUTIONS

As a class, cyclooxygenase inhibitory NSAIDs may be associated with gastrointestinal, renal and hepatic toxicity. Effects may result from decreased prostaglandin production and inhibition of the enzyme cyclooxygenase which is responsible for the formation of prostaglandins from arachidonic acid.^11–14 When NSAIDs inhibit prostaglandins that cause inflammation they may also inhibit those prostaglandins which maintain normal homeostatic function. These anti-prostaglandin effects may result in clinically significant disease in patients with underlying or pre-existing disease more often than in healthy patients.^12,14 NSAID therapy could unmask occult disease which has previously been undiagnosed due to the absence of apparent clinical signs. Patients with underlying renal disease for example, may experience exacerbation or decompensation of their renal disease while on NSAID therapy.^11–14 The use of parenteral fluids during surgery should be considered to reduce the potential risk of renal complications when using NSAIDs perioperatively.

Carprofen is an NSAID, and as with others in that class, adverse reactions may occur with its use. The most frequently reported effects have been gastrointestinal signs. Events involving suspected renal, hematologic, neurologic, dermatologic, and hepatic effects have also been reported. Patients at greatest risk for renal toxicity are those that are dehydrated, on concomitant diuretic therapy, or those with renal, cardiovascular, and/or hepatic dysfunction. Concurrent administration of potentially nephrotoxic drugs should be approached cautiously, with appropriate monitoring. Concomitant use of Rimadyl with other anti-inflammatory drugs, such as other NSAIDs or corticosteroids, should be avoided because of the potential increase of adverse reactions, including gastrointestinal ulcerations and/or perforations. Sensitivity to drug-associated adverse reactions varies with the individual patient. Dogs that have experienced adverse reactions from one NSAID may experience adverse reactions from another NSAID. Rimadyl treatment was not associated with renal toxicity or gastrointestinal ulceration in well-controlled safety studies of up to ten times the dose in healthy dogs.

Rimadyl is not recommended for use in dogs with bleeding disorders (e.g., Von Willebrand's disease), as safety has not been established in dogs with these disorders. The safe use of Rimadyl in animals less than 6 weeks of age, pregnant dogs, dogs used for breeding purposes, or in lactating bitches has not been established. Studies to determine the activity of Rimadyl when administered concomitantly with other protein-bound or similarly metabolized drugs have not been conducted. Drug compatibility should be monitored closely in patients requiring additional therapy. Such drugs commonly used include cardiac, anticonvulsant and behavioral medications. It has been suggested that treatment with carprofen may reduce the level of inhalant anesthetics needed.^15

If additional pain medication is warranted after administration of the total daily dose of Rimadyl, alternative analgesia should be considered. The use of another NSAID is not recommended. Consider appropriate washout times when switching from one NSAID to another or when switching from corticosteroid use to NSAID use.

INFORMATION FOR DOG OWNERS

Rimadyl, like other drugs of its class, is not free from adverse reactions. Owners should be advised of the potential for adverse reactions and be informed of the clinical signs associated with drug intolerance.
Adverse reactions may include decreased appetite, vomiting, diarrhea, dark or tarry stools, increased water consumption, increased urination, pale gums due to anemia, yellowing of gums, skin or white of the eye due to jaundice, lethargy, incoordination, seizure, or behavioral changes. Serious adverse reactions associated with this drug class can occur without warning and in rare situations result in death (see Adverse Reactions). Owners should be advised to discontinue Rimadyl therapy and contact their veterinarian immediately if signs of intolerance are observed. The vast majority of patients with drug related adverse reactions have recovered when the signs are recognized, the drug is withdrawn, and veterinary care, if appropriate, is initiated. Owners should be advised of the importance of periodic follow up for all dogs during administration of any NSAID.

ADVERSE REACTIONS

During investigational studies of osteoarthritis with twice daily administration of 1 mg/lb, no clinically significant adverse reactions were reported. Some clinical signs were observed during field studies (n=297) which were similar for carprofen- and placebo-treated dogs. Incidences of the following were observed in both groups: vomiting (4%), diarrhea (4%), changes in appetite (3%), lethargy (1.4%), behavioral changes (1%), and constipation (0.3%). The product vehicle served as control.

There were no serious adverse events reported during clinical field studies of osteoarthritis with once daily administration of 2 mg/lb. The following categories of abnormal health observations were reported. The product vehicle served as control.

Percentage of Dogs with Abnormal Health Observations Reported in Osteoarthritis Field Study (2 mg/lb once daily)
Observation | Rimadyl (n=129) | Placebo (n=132)
Inappetence | 1.6 | 1.5
Vomiting | 3.1 | 3.8
Diarrhea/Soft stool | 3.1 | 4.5
Behavior change | 0.8 | 0.8
Dermatitis | 0.8 | 0.8
PU/PD | 0.8 | —
SAP increase | 7.8 | 8.3
ALT increase | 5.4 | 4.5
AST increase | 2.3 | 0.8
BUN increase | 3.1 | 1.5
Bilirubinuria | 16.3 | 12.1
Ketonuria | 14.7 | 9.1

Clinical pathology parameters listed represent reports of increases from pre-treatment values; medical judgement is necessary to determine clinical relevance.

During investigational studies of surgical pain for the caplet formulation, no clinically significant adverse reactions were reported. The product vehicle served as control.

Percentage of Dogs with Abnormal Health Observations Reported in Surgical Pain Field Studies with Caplets (2 mg/lb once daily)
Observation [A single dog may have experienced more than one occurrence of an event.] | Rimadyl (n=148) | Placebo (n=149)
Vomiting | 10.1 | 13.4
Diarrhea/soft stool | 6.1 | 6.0
Ocular disease | 2.7 | 0
Inappetence | 1.4 | 0
Dermatitis/skin lesion | 2.0 | 1.3
Dysrhythmia | 0.7 | 0
Apnea | 1.4 | 0
Oral/periodontal disease | 1.4 | 0
Pyrexia | 0.7 | 1.3
Urinary tract disease | 1.4 | 1.3
Wound drainage | 1.4 | 0

* A single dog may have experienced more than one occurrence of an event.

Post-Approval Experience

Although not all adverse reactions are reported, the following adverse reactions are based on voluntary post-approval adverse drug experience reporting. The categories of adverse reactions are listed in decreasing order of frequency by body system.

Gastrointestinal: Vomiting, diarrhea, constipation, inappetence, melena, hematemesis, gastrointestinal ulceration, gastrointestinal bleeding, pancreatitis.

Hepatic: Inappetence, vomiting, jaundice, acute hepatic toxicity, hepatic enzyme elevation, abnormal liver function test(s), hyperbilirubinemia, bilirubinuria, hypoalbuminemia. Approximately one-fourth of hepatic reports were in Labrador Retrievers.

Neurologic: Ataxia, paresis, paralysis, seizures, vestibular signs, disorientation.

Urinary: Hematuria, polyuria, polydipsia, urinary incontinence, urinary tract infection, azotemia, acute renal failure, tubular abnormalities including acute tubular necrosis, renal tubular acidosis, glucosuria.

Behavioral: Sedation, lethargy, hyperactivity, restlessness, aggressiveness.

Hematologic: Immune-mediated hemolytic anemia, immune-mediated thrombocytopenia, blood loss anemia, epistaxis.

Dermatologic: Pruritus, increased shedding, alopecia, pyotraumatic moist dermatitis (hot spots), necrotizing panniculitis/vasculitis, ventral ecchymosis.

Immunologic or hypersensitivity: Facial swelling, hives, erythema.

In rare situations, death has been associated with some of the adverse reactions listed above.

To report a suspected adverse reaction call 1-888-963-8471.

DOSAGE AND ADMINISTRATION

Always provide Client Information Sheet with prescription. Carefully consider the potential benefits and risk of Rimadyl and other treatment options before deciding to use Rimadyl. Use the lowest effective dose for the shortest duration consistent with individual response. The recommended dosage for oral administration to dogs is 2 mg/lb (4.4 mg/kg) of body weight daily. The total daily dose may be administered as 2 mg/lb of body weight once daily or divided and administered as 1 mg/lb (2.2 mg/kg) twice daily. For the control of postoperative pain, administer approximately 2 hours before the procedure. Caplets are scored and dosage should be calculated in half-caplet increments.

EFFECTIVENESS

Confirmation of the effectiveness of Rimadyl for the relief of pain and inflammation associated with osteoarthritis, and for the control of postoperative pain associated with soft tissue and orthopedic surgeries was demonstrated in 5 placebo-controlled, masked studies examining the anti-inflammatory and analgesic effectiveness of Rimadyl caplets in various breeds of dogs.

Separate placebo-controlled, masked, multicenter field studies confirmed the anti-inflammatory and analgesic effectiveness of Rimadyl caplets when dosed at 2 mg/lb once daily or when divided and administered at 1 mg/lb twice daily. In these two field studies, dogs diagnosed with osteoarthritis showed statistically significant overall improvement based on lameness evaluations by the veterinarian and owner observations when administered Rimadyl at labeled doses.

Separate placebo-controlled, masked, multicenter field studies confirmed the effectiveness of Rimadyl caplets for the control of postoperative pain when dosed at 2 mg/lb once daily in various breeds of dogs. In these studies, dogs presented for ovariohysterectomy, cruciate repair and aural surgeries were administered Rimadyl preoperatively and for a maximum of 3 days (soft tissue) or 4 days (orthopedic) postoperatively. In general, dogs administered Rimadyl showed statistically significant improvement in pain scores compared to controls.

ANIMAL SAFETY

Laboratory studies in unanesthetized dogs and clinical field studies have demonstrated that Rimadyl is well tolerated in dogs after oral administration.

In target animal safety studies, Rimadyl was administered orally to healthy Beagle dogs at 1, 3, and 5 mg/lb twice daily (1, 3 and 5 times the recommended total daily dose) for 42 consecutive days with no significant adverse reactions. Serum albumin for a single female dog receiving 5 mg/lb twice daily decreased to 2.1 g/dL after 2 weeks of treatment, returned to the pre-treatment value (2.6 g/dL) after 4 weeks of treatment, and was 2.3 g/dL at the final 6-week evaluation. Over the 6-week treatment period, black or bloody stools were observed in 1 dog (1 incident) treated with 1 mg/lb twice daily and in 1 dog (2 incidents) treated with 3 mg/lb twice daily. Redness of the colonic mucosa was observed in 1 male that received 3 mg/lb twice daily.

Two of 8 dogs receiving 10 mg/lb orally twice daily (10 times the recommended total daily dose) for 14 days exhibited hypoalbuminemia. The mean albumin level in the dogs receiving this dose was lower (2.38 g/dL) than each of 2 placebo control groups (2.88 and 2.93 g/dL, respectively). Three incidents of black or bloody stool were observed in 1 dog. Five of 8 dogs exhibited reddened areas of duodenal mucosa on gross pathologic examination. Histologic examination of these areas revealed no evidence of ulceration, but did show minimal congestion of the lamina propria in 2 of the 5 dogs.

In separate safety studies lasting 13 and 52 weeks, respectively, dogs were administered orally up to 11.4 mg/lb/day (5.7 times the recommended total daily dose of 2 mg/lb) of carprofen. In both studies, the drug was well tolerated clinically by all of the animals. No gross or histologic changes were seen in any of the treated animals. In both studies, dogs receiving the highest doses had average increases in serum L-alanine aminotransferase (ALT) of approximately 20 IU.

In the 52 week study, minor dermatologic changes occurred in dogs in each of the treatment groups but not in the control dogs. The changes were described as slight redness or rash and were diagnosed as non-specific dermatitis. The possibility exists that these mild lesions were treatment related, but no dose relationship was observed.

Clinical field studies were conducted with 549 dogs of different breeds at the recommended oral doses for 14 days (297 dogs were included in a study evaluating 1 mg/lb twice daily and 252 dogs were included in a separate study evaluating 2 mg/lb once daily). In both studies the drug was clinically well tolerated and the incidence of clinical adverse reactions for Rimadyl-treated animals was no higher than placebo-treated animals (placebo contained inactive ingredients found in Rimadyl). For animals receiving 1 mg/lb twice daily, the mean post-treatment serum ALT values were 11 IU greater and 9 IU less than pre-treatment values for dogs receiving Rimadyl and placebo, respectively. Differences were not statistically significant. For animals receiving 2 mg/lb once daily, the mean post-treatment serum ALT values were 4.5 IU greater and 0.9 IU less than pre-treatment values for dogs receiving Rimadyl and placebo, respectively. In the latter study, 3 Rimadyl-treated dogs developed a 3-fold or greater increase in (ALT) and/or (AST) during the course of therapy. One placebo-treated dog had a greater than 2-fold increase in ALT. None of these animals showed clinical signs associated with laboratory value changes. Changes in the clinical laboratory values (hematology and clinical chemistry) were not considered clinically significant. The 1 mg/lb twice daily course of therapy was repeated as needed at 2-week intervals in 244 dogs, some for as long as 5 years.

Clinical field studies were conducted in 297 dogs of different breeds undergoing orthopedic or soft tissue surgery. Dogs were administered 2 mg/lb of Rimadyl two hours prior to surgery then once daily, as needed for 2 days (soft tissue surgery) or 3 days (orthopedic surgery). Rimadyl was well tolerated when used in conjunction with a variety of anesthetic-related drugs. The type and severity of abnormal health observations in Rimadyl- and placebo-treated animals were approximately equal and few in number (see Adverse Reactions). The most frequent abnormal health observation was vomiting and was observed at approximately the same frequency in Rimadyl- and placebo-treated animals. Changes in clinicopathologic indices of hematopoietic, renal, hepatic, and clotting function were not clinically significant. The mean post-treatment serum ALT values were 7.3 IU and 2.5 IU less than pre-treatment values for dogs receiving Rimadyl and placebo, respectively. The mean post-treatment AST values were 3.1 IU less for dogs receiving Rimadyl and 0.2 IU greater for dogs receiving placebo.

STORAGE

Store at controlled room temperature 15°–30°C (59°–86°F).

HOW SUPPLIED

Rimadyl caplets are scored, and contain 25 mg, 75 mg, or 100 mg of carprofen per caplet. Each caplet size is packaged in bottles containing 30, 60, or 180 caplets, or blister packs containing 4 caplets.

REFERENCES

1. Baruth H, et al: In Anti-Inflammatory and Anti-Rheumatic Drugs, Vol. II, Newer Anti-Inflammatory Drugs, Rainsford KD, ed. CRC Press, Boca Raton, pp. 33–47, 1986.

2. Vane JR, Botting RM: Mechanism of action of anti-inflammatory drugs. Scand J Rheumatol 25:102, pp. 9–21.

3. Grossman CJ, Wiseman J, Lucas FS, et al: Inhibition of constitutive and inducible cyclooxygenase activity in human platelets and mononuclear cells by NSAIDs and Cox-2 inhibitors. Inflammation Research 44:253–257, 1995.

4. Ricketts AP, Lundy KM, Seibel SB: Evaluation of selective inhibition of canine cyclooxygenase 1 and 2 by carprofen and other nonsteroidal anti-inflammatory drugs. Am J Vet Res 59:11, pp. 1441–1446, November 1998.

5. Ceuppens JL, et al: Non-steroidal anti-inflammatory agents inhibit the synthesis of IgM rheumatoid factor in vitro. Lancet 1:528, 1982.

6. Ceuppens JL, et al: Endogenous prostaglandin E2 enhances polyclonal immunoglobulin production by ionically inhibiting T suppressor cell activity. Cell Immunol 70:41, 1982.

7. Schleimer RP, et al: The effects of prostaglandin synthesis inhibition on the immune response. Immunopharmacology 3:205, 1981.

8. Leung KH, et al: Modulation of the development of cell mediated immunity: possible roles of the products of cyclooxygenase and lipoxygenase pathways of arachidonic acid metabolism. Int J Immunopharmacology 4:195, 1982.

9. Veit BC: Immunoregulatory activity of cultured-induced suppressor macrophages. Cell Immunol 72:14, 1982.

10. Schmitt M, et al: Biopharmaceutical evaluation of carprofen following single intravenous, oral, and rectal doses in dogs. Biopharm Drug Dispos 11(7):585–94, 1990.

11. Kore AM: Toxicology of nonsteroidal anti-inflammatory drugs. Veterinary Clinics of North America, Small Animal Practice 20, March 1990.

12. Binns SH: Pathogenesis and pathophysiology of ischemic injury in cases of acute renal failure. Compend for Cont Ed 16:1, January 1994.

13. Boothe DM: Prostaglandins: Physiology and clinical implications. Compend for Cont Ed 6:11, November 1984.

14. Rubin SI: Nonsteroidal anti-inflammatory drugs, prostaglandins, and the kidney. JAVMA 188:9, May 1986.

15. Ko CH, Lange DN, Mandsager RE, et al: Effects of butorphanol and carprofen on the minimal alveolar concentration of isoflurane in dogs. JAVMA 217:1025-1028, 2000.

For a copy of the Material Safety Data Sheet (MSDS) call 1-888-963-8471. To report adverse reactions call Zoetis at 1-888-963-8471.

Approved by FDA under NADA # 141-053

Zoetis
Distributed by:
Zoetis Inc.
Kalamazoo, MI 49007
40028070
Revised: May 2019

Dog Owner Information about RIMADYL® Caplets (carprofen tablets)

Rimadyl® (pronounced "Rim-a-dill")
for Osteoarthritis and Post-Surgical Pain
Generic name: carprofen ("car-prō-fen")

This summary contains important information about Rimadyl. You should read this information before you start giving your dog Rimadyl and review it each time the prescription is refilled. This sheet is provided only as a summary and does not take the place of instructions from your veterinarian. Talk to your veterinarian if you do not understand any of this information or if you want to know more about Rimadyl.

What is Rimadyl?

Rimadyl is a nonsteroidal anti-inflammatory drug (NSAID) that is used to reduce pain and inflammation (soreness) due to osteoarthritis and pain following surgery in dogs. Rimadyl is a prescription drug for dogs. It is available as a caplet and chewable tablet and is given to dogs by mouth.

Osteoarthritis (OA) is a painful condition caused by "wear and tear" of cartilage and other parts of the joints that may result in the following changes or signs in your dog:

- Limping or lameness
- Decreased activity or exercise (reluctance to stand, climb stairs, jump or run, or difficulty in performing these activities)
- Stiffness or decreased movement of joints

To control surgical pain (e.g. for surgeries such as spays, ear procedures or orthopedic repairs) your veterinarian may administer Rimadyl before the procedure and recommend that your dog be treated for several days after going home.

What kind of results can I expect when my dog is on Rimadyl?

While Rimadyl is not a cure for osteoarthritis, it can relieve the pain and inflammation of OA and improve your dog's mobility.

- Response varies from dog to dog but can be quite dramatic.
- In most dogs, improvement can be seen in a matter of days.
- If Rimadyl is discontinued or not given as directed, your dog's pain and inflammation may come back.

Who should not take Rimadyl?

Your dog should not be given Rimadyl if he/she:

- Has had an allergic reaction to carprofen, the active ingredient of Rimadyl.
- Has had an allergic reaction to aspirin or other NSAIDs (for example deracoxib, etodolac, firocoxib, meloxicam, phenylbutazone or tepoxalin) such as hives, facial swelling, or red or itchy skin.

Rimadyl should be given to dogs only. Cats should not be given Rimadyl. Call your veterinarian immediately if your cat receives Rimadyl. People should not take Rimadyl. Keep Rimadyl and all medicines out of reach of children. Call your physician immediately if you accidentally take Rimadyl.

How to give Rimadyl to your dog.

Rimadyl should be given according to your veterinarian's instructions. Your veterinarian will tell you what amount of Rimadyl is right for your dog and for how long it should be given. Rimadyl should be given by mouth and may be given with or without food.

What to tell/ask your veterinarian before giving Rimadyl.

Talk to your veterinarian about:

- The signs of OA you have observed (for example limping, stiffness).
- The importance of weight control and exercise in the management of OA.
- What tests might be done before Rimadyl is prescribed.
- How often your dog may need to be examined by your veterinarian.
- The risks and benefits of using Rimadyl.

Tell your veterinarian if your dog has ever had the following medical problems:

- Experienced side effects from Rimadyl or other NSAIDs, such as aspirin
- Digestive upset (vomiting and/or diarrhea)
- Liver disease
- Kidney disease
- A bleeding disorder (for example, Von Willebrand's disease)

Tell your veterinarian about:

- Any other medical problems or allergies that your dog has now or has had.
- All medicines that you are giving your dog or plan to give your dog, including those you can get without a prescription.

Tell your veterinarian if your dog is:

- Pregnant, nursing or if you plan to breed your dog.

What are the possible side effects that may occur in my dog during Rimadyl therapy?

Rimadyl, like other drugs, may cause some side effects. Serious but rare side effects have been reported in dogs taking NSAIDs, including Rimadyl. Serious side effects can occur with or without warning and in rare situations result in death.

The most common NSAID-related side effects generally involve the stomach (such as bleeding ulcers), and liver or kidney problems. Look for the following side effects that can indicate your dog may be having a problem with Rimadyl or may have another medical problem:

- Decrease or increase in appetite
- Vomiting
- Change in bowel movements (such as diarrhea, or black, tarry or bloody stools)
- Change in behavior (such as decreased or increased activity level, incoordination, seizure or aggression)
- Yellowing of gums, skin, or whites of the eyes (jaundice)
- Change in drinking habits (frequency, amount consumed)
- Change in urination habits (frequency, color, or smell)
- Change in skin (redness, scabs, or scratching)

It is important to stop therapy and contact your veterinarian immediately if you think your dog has a medical problem or side effect from Rimadyl therapy. If you have additional questions about possible side effects, talk to your veterinarian.

Can Rimadyl be given with other medicines?

Rimadyl should not be given with other NSAIDs (for example, aspirin, deracoxib, etodolac, firocoxib, meloxicam, tepoxalin) or steroids (for example, cortisone, dexamethasone, prednisone, triamcinolone).

Tell your veterinarian about all medicines you have given your dog in the past, and any medicines that you are planning to give with Rimadyl. This should include other medicines that you can get without a prescription. Your veterinarian may want to check that all of your dog's medicines can be given together.

What do I do in case my dog eats more than the prescribed amount of Rimadyl?

Contact your veterinarian immediately if your dog eats more than the prescribed amount of Rimadyl.

What else should I know about Rimadyl?

This sheet provides a summary of information about Rimadyl. If you have any questions or concerns about Rimadyl, or osteoarthritis, or postoperative pain, talk to your veterinarian.

As with all prescribed medicines, Rimadyl should only be given to the dog for which it was prescribed. It should be given to your dog only for the condition for which it was prescribed.

It is important to periodically discuss your dog's response to Rimadyl at regular check ups. Your veterinarian will best determine if your dog is responding as expected and if your dog should continue receiving Rimadyl.

To report a suspected adverse reaction call Zoetis at 1-888-963-8471.

Approved by FDA under NADA # 141-053

zoetis

Distributed by:
Zoetis Inc.
Kalamazoo, MI 49007

www.rimadyl.com

PRINCIPAL DISPLAY PANEL - 25 mg Caplet Bottle Label

RIMADYL®
(carprofen tablets)

25 mg

30 caplets

For oral use in dogs only

Caution: Federal law restricts this drug
to use by or on the order of a licensed
veterinarian.

Non-steroidal
anti-inflammatory drug

Approved by FDA under NADA # 141-053

zoetis

PRINCIPAL DISPLAY PANEL - 75 mg Caplet Bottle Label

RIMADYL®
(carprofen tablets)

75 mg

30 caplets

For oral use in dogs only

Caution: Federal law restricts this drug
to use by or on the order of a licensed
veterinarian.

Non-steroidal
anti-inflammatory drug

Approved by FDA under NADA # 141-053

zoetis

PRINCIPAL DISPLAY PANEL - 100 mg Caplet Bottle Label

RIMADYL®
(carprofen tablets)

100 mg

30 caplets

For oral use in dogs only

Caution: Federal law restricts this drug
to use by or on the order of a licensed
veterinarian.

Non-steroidal
anti-inflammatory drug

Approved by FDA under NADA # 141-053

zoetis